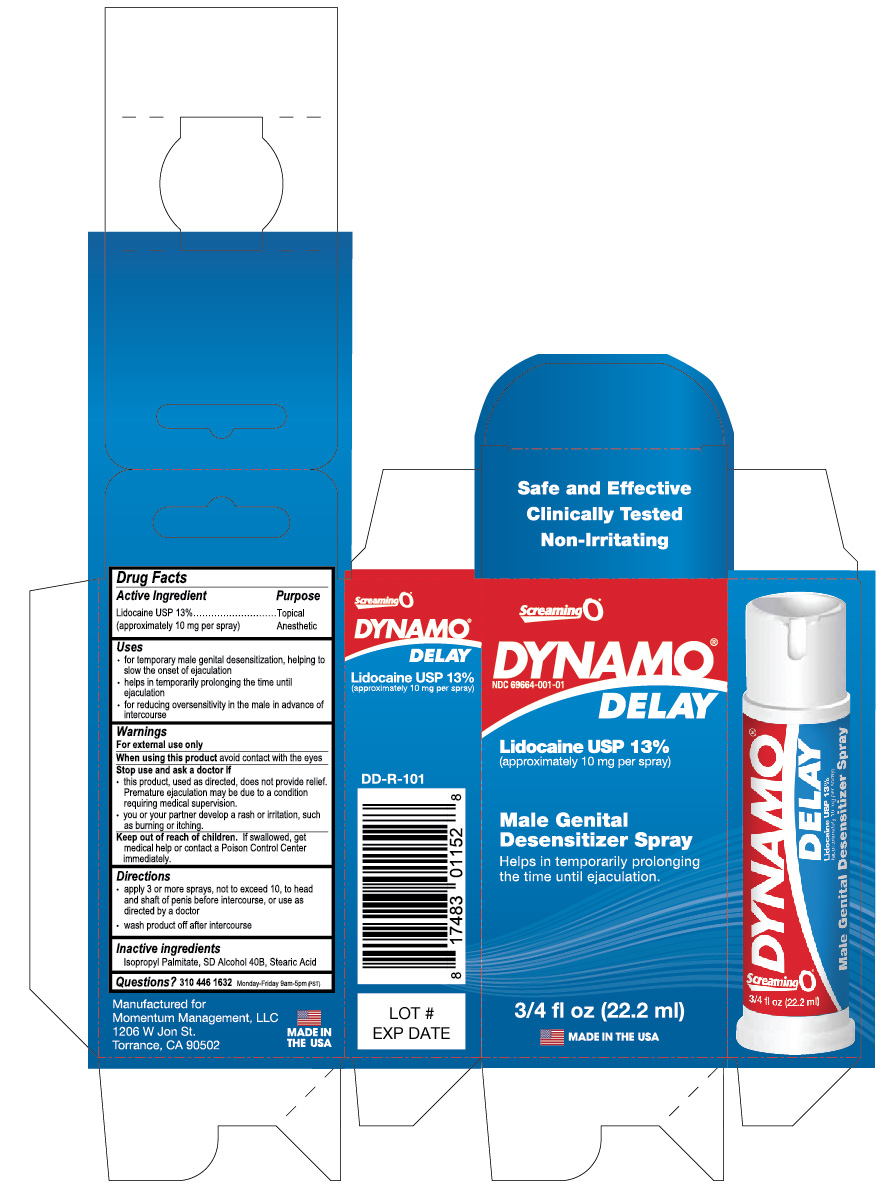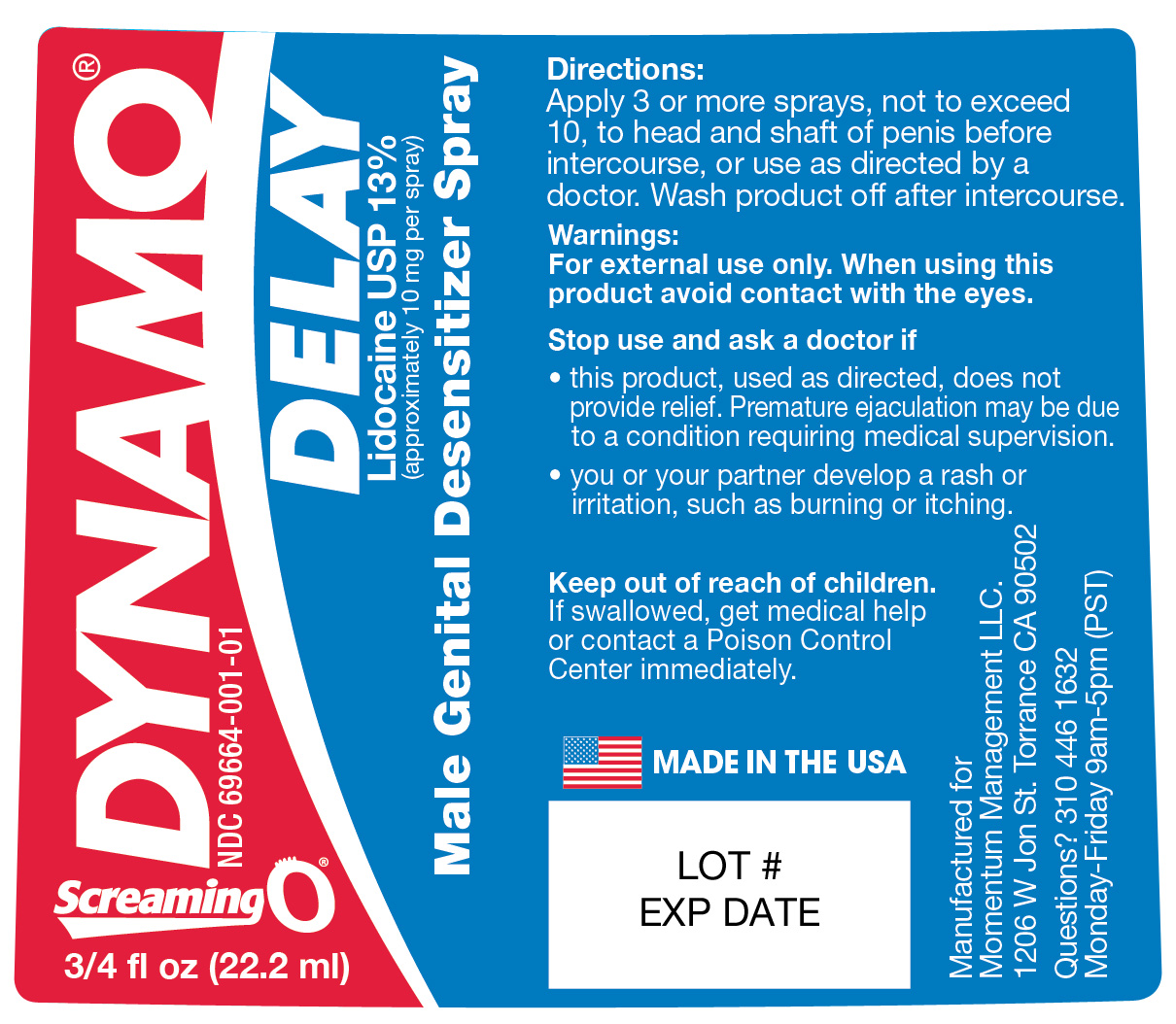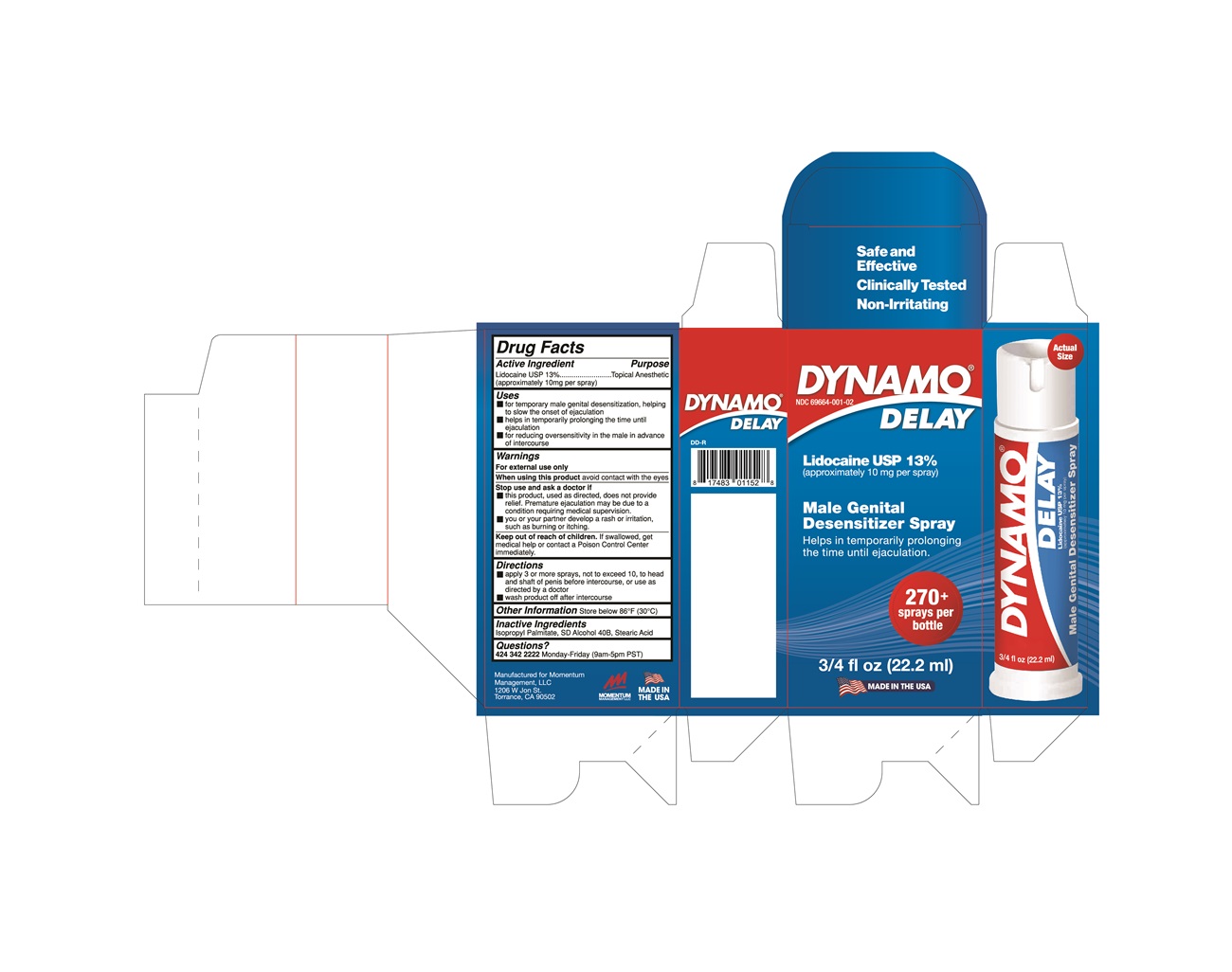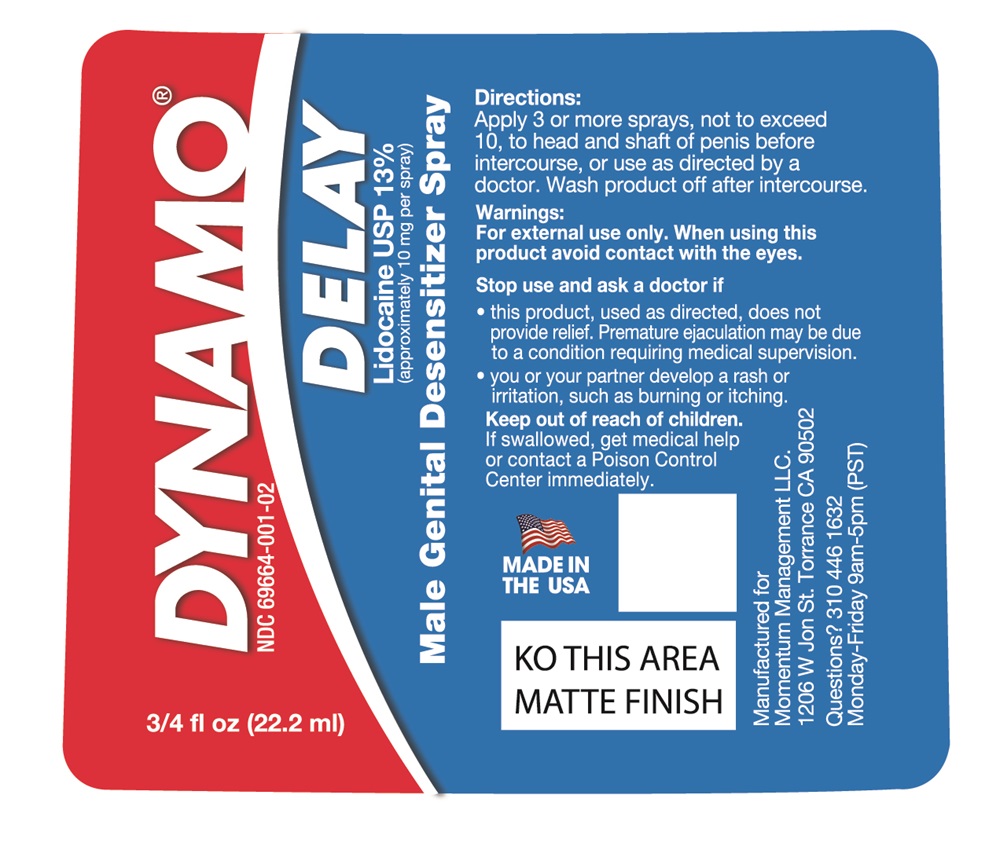 DRUG LABEL: DYNAMO DELAY
NDC: 69664-001 | Form: SPRAY
Manufacturer: Momentum Management LLC
Category: otc | Type: Human OTC Drug Label
Date: 20251003

ACTIVE INGREDIENTS: LIDOCAINE 10 mg/0.08 mL
INACTIVE INGREDIENTS: ISOPROPYL PALMITATE; ALCOHOL; STEARIC ACID

BU05-Delay Spray For Men

Active Ingredient

Lidocaine USP 13%

(approximately 10 mg per spray)

Purpose

Topical Anesthetic

Uses

- for temporary male genital desensitization, helping to slow the onset of ejaculation
- helps in temporarily prolonging the time until ejaculation
- for reducing oversensitivity in the male in advance of intercourse

Warnings

For external use only

When using this product

avoid contact with the eyes

Stop use and ask a doctor if:

- this product, used as directed, does not provide relief. Premature ejaculation may be due to a condition requiring medical supervision.
- you or your partner develop a rash or irritation, such as burning or itching.

Keep out of reach of children

If swallowed, get medical help or contact a Poison Control Center immediately

Directions

- apply 3 or more sprays, not to exceed 10, to head and shaft of penis before intercourse, or use as directed by a doctor.
- wash product off after intercourse

Other Information

Store below 86°F (30°C)

Inactive Ingredients

Isopropyl Palmitate, SD Alcohol 40B, Stearic Acid

Questions?

310 446 1632 Monday - Friday 9am-5pm(PST)

Manufactured for

Momentum Management LLC

1206 W Jon St

Torrance, CA 90502

Principal Display Panel

Dynamo Delay

NDC 69664-001-02

Lidocaine USP 13%

(appromixately 10 mg per spray)

Male Genital Desensitizer Spray

Helps in temporarily prolonging the time until ejaculation

270+ sprays per bottle

3/4 fl oz (22.2mL)

Made in the USA

Bottle Label: